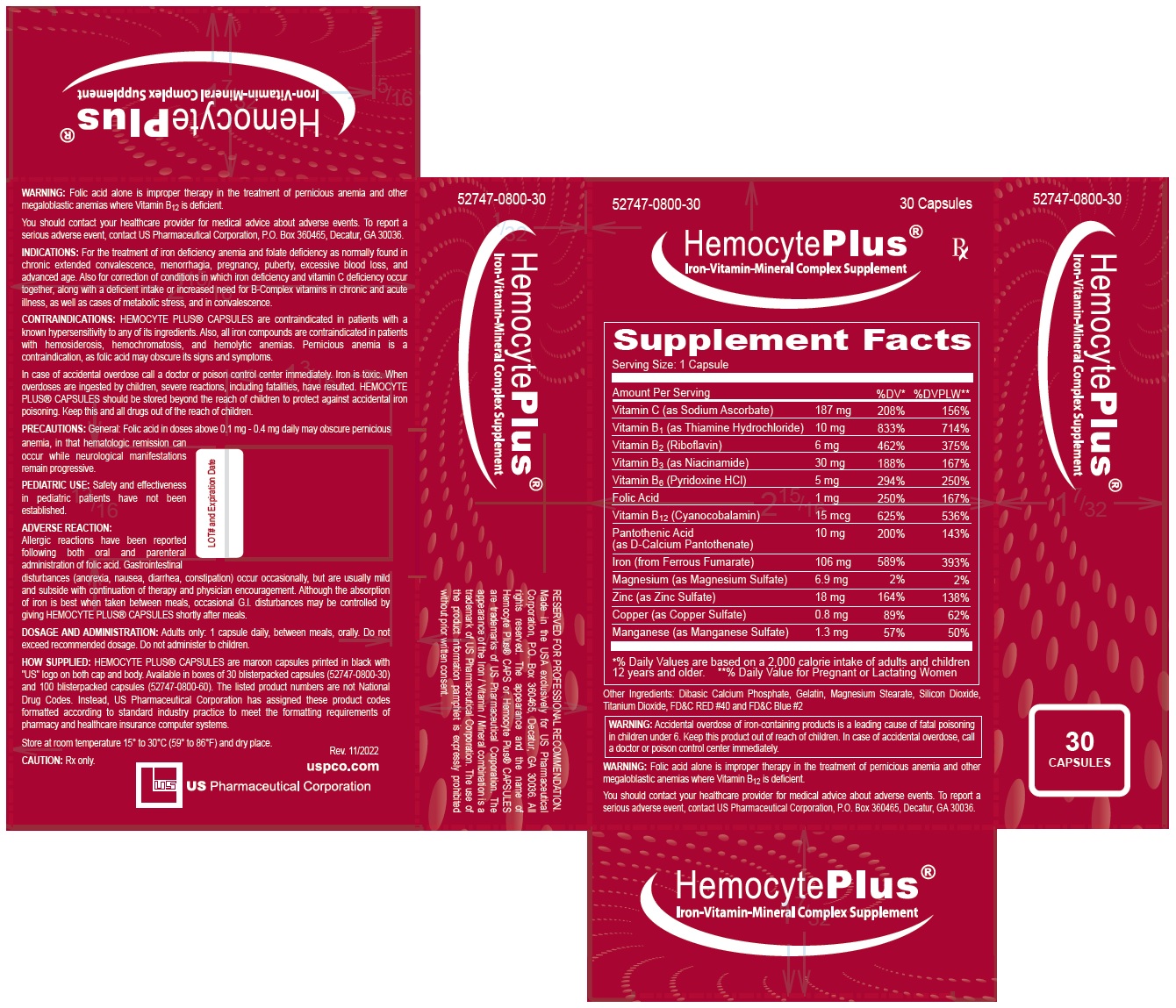 DRUG LABEL: Hemocyte Plus
NDC: 52747-800 | Form: CAPSULE
Manufacturer: U.S. Pharmaceutical Corporation
Category: other | Type: DIETARY SUPPLEMENT
Date: 20230614

ACTIVE INGREDIENTS: SODIUM ASCORBATE 187 mg/1 1; THIAMINE MONONITRATE 10 mg/1 1; RIBOFLAVIN 6 mg/1 1; NIACIN 30 mg/1 1; PYRIDOXINE HYDROCHLORIDE 5 mg/1 1; FOLIC ACID 1 mg/1 1; CYANOCOBALAMIN 0.015 mg/1 1; PANTOTHENIC ACID 10 mg/1 1; FERROUS FUMARATE 106 mg/1 1; MAGNESIUM SULFATE, UNSPECIFIED FORM 6.9 mg/1 1; ZINC SULFATE, UNSPECIFIED FORM 18 mg/1 1; CUPRIC SULFATE 0.8 mg/1 1; MANGANESE SULFATE 1.3 mg/1 1
INACTIVE INGREDIENTS: GELATIN, UNSPECIFIED; MAGNESIUM STEARATE; ANHYDROUS DIBASIC CALCIUM PHOSPHATE; SILICON DIOXIDE; TITANIUM DIOXIDE; FD&C RED NO. 40; FD&C BLUE NO. 2

HemocytePlus®

STATEMENT OF IDENTITY

Supplement Facts
Serving Size: 1 Capsule
Amount Per Serving |  | %DV* | %DVPLW**
Vitamin C (as Sodium Ascorbate) | 187 mg | 208% | 156%
Vitamin B1 (as Thiamine Hydrochloride) | 10 mg | 833% | 714%
Vitamin B2 (Riboflavin) | 6 mg | 462% | 375%
Vitamin B3 (as Niacinamide) | 30 mg | 188% | 167%
Vitamin B6 (Pyridoxine HCl) | 5 mg | 294% | 250%
Folic Acid | 1 mg | 250% | 167%
Vitamin B12 (Cyanocobalamin) | 15 mcg | 625% | 536%
Pantothenic Acid (as D-Calcium Pantothenate) | 10 mg | 200% | 143%
Iron (from Ferrous Fumarate) | 106 mg | 589% | 393%
Magnesium (as Magnesium Sulfate) | 6.9 mg | 2% | 2%
Zinc (as Zinc Sulfate) | 18 mg | 164% | 138%
Copper (as Copper Sulfate) | 0.8 mg | 89% | 62%
Manganese (as Manganese Sulfate) | 1.3 mg | 57% | 50%
*% Daily Values are based on a 2,000 calorie intake of adults and children 12 years and older. **% Daily Value for Pregnant or Lactating Women

Other Ingredients: Dibasic Calcium Phosphate, Gelatin, Magnesium Stearate, Silicon Dioxide, Titanium Dioxide, FD&C RED #40 and FD&C Blue #2

INDICATIONS: For the treatment of iron deficiency anemia and folate deficiency as normally found in chronic extended convalescence, menorrhagia, pregnancy, puberty, excessive blood loss, and advanced age. Also for correction of conditions in which iron deficiency and vitamin C deficiency occur together, along with a deficient intake or increased need for B-Complex vitamins in chronic and acute illness, as well as cases of metabolic stress, and in convalescence.

CONTRAINDICATIONS: HEMOCYTE PLUS® CAPSULES are contraindicated in patients with a known hypersensitivity to any of its ingredients. Also, all iron compounds are contraindicated in patients with hemosiderosis, hemochromatosis, and hemolytic anemias. Pernicious anemia is a contraindication, as folic acid may obscure its signs and symptoms.

In case of accidental overdose call a doctor or poison control center immediately. Iron is toxic. When overdoses are ingested by children, severe reactions, including fatalities, have resulted. HEMOCYTE PLUS® CAPSULES should be stored beyond the reach of children to protect against accidental iron poisoning. Keep this and all drugs out of the reach of children.

WARNINGS

WARNING: Accidental overdose of iron-containing products is a leading cause of fatal poisoning in children under 6. Keep this product out of reach of children. In case of accidental overdose, call a doctor or poison control center immediately.

WARNING: Folic acid alone is improper therapy in the treatment of pernicious anemia and other megaloblastic anemias where Vitamin B12 is deficient.

You should contact your healthcare provider for medical advice about adverse events. To report a serious adverse event, contact US Pharmaceutical Corporation, P.O. Box 360465, Decatur, GA 30036.

PRECAUTIONS

PRECAUTIONS: General: Folic acid in doses above 0.1 mg - 0.4 mg daily may obscure pernicious anemia, in that hematologic remission can occur while neurological manifestations remain progressive.

PEDIATRIC USE: Safety and effectiveness in pediatric patients have not been established.

ADVERSE REACTION:
Allergic reactions have been reported following both oral and parenteral administration of folic acid. Gastrointestinal disturbances (anorexia, nausea, diarrhea, constipation) occur occasionally, but are usually mild and subside with continuation of therapy and physician encouragement. Although the absorption of iron is best when taken between meals, occasional G.I. disturbances may be controlled by giving HEMOCYTE PLUS® CAPSULES shortly after meals.

DOSAGE AND ADMINISTRATION: Adults only: 1 capsule daily, between meals, orally. Do not exceed recommended dosage. Do not administer to children.

HOW SUPPLIED: HEMOCYTE PLUS® CAPSULES are maroon capsules printed in black with "US" logo on both cap and body. Available in boxes of 30 blisterpacked capsules (52747-0800-30) and 100 blisterpacked capsules (52747-0800-60). The listed product numbers are not National Drug Codes. Instead, US Pharmaceutical Corporation has assigned these product codes formatted according to standard industry practice to meet the formatting requirements of pharmacy and healthcare insurance computer systems.

SAFE HANDLING WARNING

Store at room temperature 15° to 30°C (59° to 86°F) and dry place.

CAUTION: Rx only.

Rev. 11/2022

uspco.com

HEALTH CLAIM

Iron-Vitamin-Mineral Complex Supplement

RESERVED FOR PROFESSIONAL RECOMMENDATION. Made in the USA exclusively for US Pharmaceutical Corporation, P.O. Box 360465, Decatur, GA 30036. All rights reserved. The appearance and the name of Hemocyte Plus® CAPS or Hemocyte Plus® CAPSULES are trademarks of US Pharmaceutical Corporation. The appearance of the Iron / Vitamin / Mineral combination is a trademark of US Pharmaceutical Corporation. The use of the product information pamphlet is expressly prohibited without prior written consent.